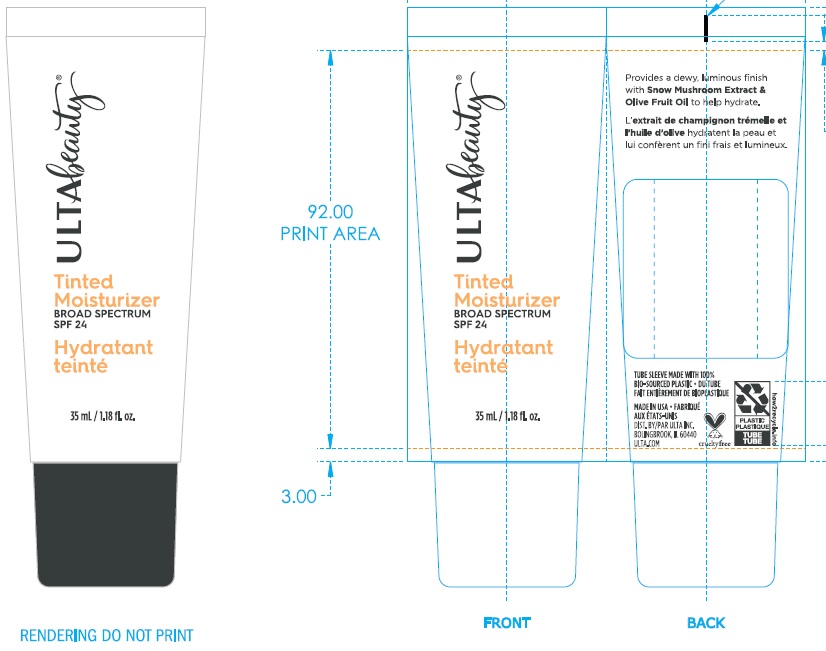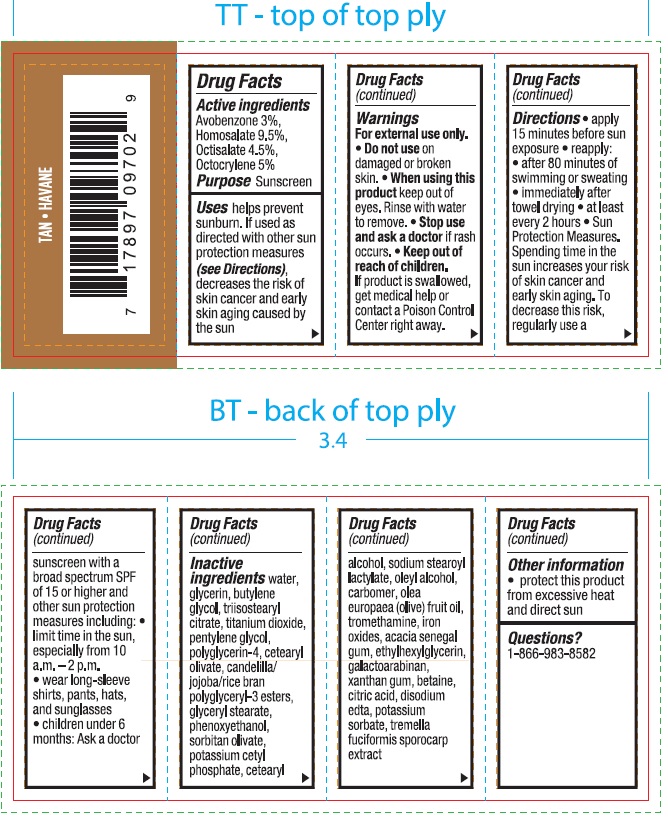 DRUG LABEL: Ulta Beauty Tinted Moisturizer Cream Spf 24 Tan
NDC: 68577-035 | Form: CREAM
Manufacturer: Cosmax Usa, Corporation
Category: otc | Type: HUMAN OTC DRUG LABEL
Date: 20241226

ACTIVE INGREDIENTS: AVOBENZONE 30 mg/1 mL; HOMOSALATE 95 mg/1 mL; OCTISALATE 45 mg/1 mL; OCTOCRYLENE 50 mg/1 mL
INACTIVE INGREDIENTS: GLYCERIN; BUTYLENE GLYCOL; TRIISOSTEARYL CITRATE; TITANIUM DIOXIDE; PENTYLENE GLYCOL; POLYGLYCERIN-4; CETEARYL OLIVATE; GLYCERYL MONOSTEARATE; PHENOXYETHANOL; SORBITAN OLIVATE; POTASSIUM CETYL PHOSPHATE; CETOSTEARYL ALCOHOL; SODIUM STEAROYL LACTYLATE; OLEYL ALCOHOL; CARBOMER HOMOPOLYMER, UNSPECIFIED TYPE; OLIVE OIL; TROMETHAMINE; FERRIC OXIDE RED; ACACIA; ETHYLHEXYLGLYCERIN; GALACTOARABINAN; XANTHAN GUM; BETAINE; CITRIC ACID MONOHYDRATE; EDETATE DISODIUM ANHYDROUS; POTASSIUM SORBATE; TREMELLA FUCIFORMIS FRUITING BODY; WATER

Ulta Beauty Tinted Moisturizer Cream Spf 24 Tan

Active ingredients

Avobenzone 3%

Homosalate 9.5%

Octisalate 4.5%

Octocrylene 5%

Purpose

Sunscreen

Uses

helps prevent sunburn. If used as directed with other sun protection measures (see Directions), decreases the risk of skin cancer and early skin aging caused by the sun

Warnings

For external use only.

Do not use

- on damaged or broken skin.

When using this product

- keep out of eyes. Rinse with water to remove.

Stop ues and ask a doctor

- if rash occurs.

Keep out of reach of children.

If product is swallowed, get medical help or contact a Poison Control Center right away.

Directions

- apply 15 minutes before sun exposure
- reapply:
- after 80 minutes of swimming or sweating
- immediately after towel drying
- at least every 2 hours
- Sun Protection Measures. Spending time in the sun increases your risk of skin cancer and early skin aging. To decrease this risk, regularly use a sunscreen with a broad spectrum SPF of 15 or higher and other sun protection measures including:
- limit time in the sun, especially from 10 a.m. - 2 p.m.
- wear long-sleeve shirts, pants, hats, and sunglasses
- children under 6 months: Ask a doctor

Inactive ingredients

water, glycerin, butylene glycol, triisostearyl citrate, titanium dioxide, pentylene glycol, polyglycerin-4, cetearyl olivate, candelilla/jojoba/rice bran polyglyceryl-3 esters, glyceryl stearate, phenoxyethanol, sorbitan olivate, potassium cetyl phosphate, cetearyl alcohol, sodium stearoyl latylate, oleyl alcohol, carbomer, olea europaea (olive) fruit oil, tromethamine, iron oxides, acacia senegal gum, ethylhexylglycerin, galactoarabinan, xanthan gum, betaine, citric acid, disodium edta, potassium sorbate, tremella fuciformis sporocarp extract

Other information

- protect this product from excessive heat and direct sun

Questions?

1-866-983-8582